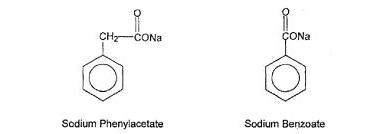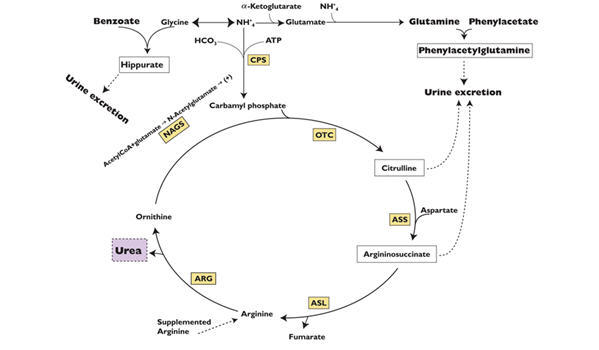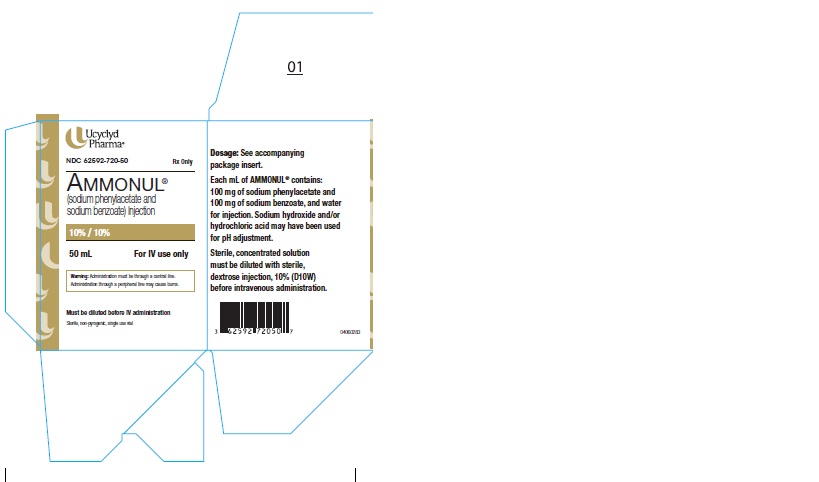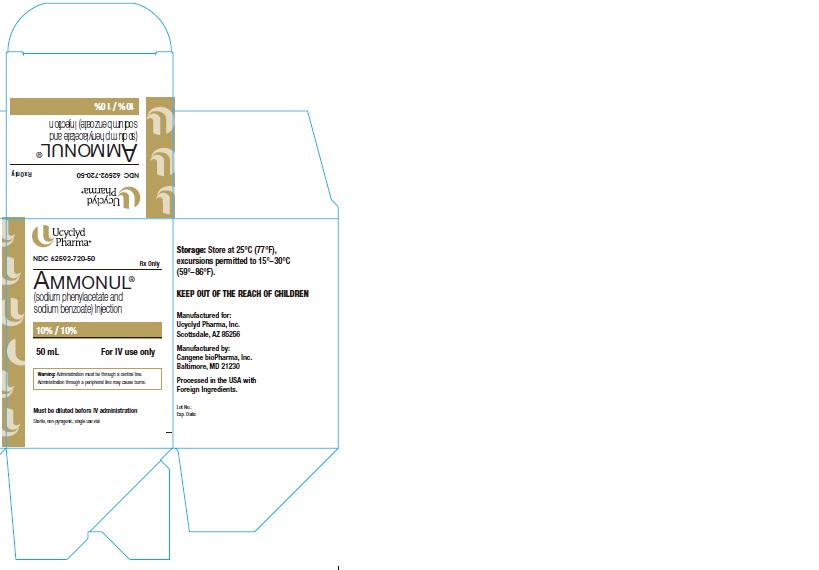 DRUG LABEL: Ammonul
NDC: 62592-720 | Form: INJECTION, SOLUTION, CONCENTRATE
Manufacturer: Ucyclyd Pharma Inc.
Category: prescription | Type: HUMAN PRESCRIPTION DRUG LABEL
Date: 20180112

ACTIVE INGREDIENTS: SODIUM PHENYLACETATE 100 mg/1 mL; SODIUM BENZOATE 100 mg/1 mL
INACTIVE INGREDIENTS: WATER; SODIUM HYDROXIDE; HYDROCHLORIC ACID

HIGHLIGHTS OF PRESCRIBING INFORMATION

These highlights do not include all the information needed to use AMMONUL® safely and effectively. See full prescribing information for AMMONUL®
AMMONUL® (sodium phenylacetate and sodium benzoate) injection, for
intravenous use
Initial U.S. Approval: 1987

1 INDICATIONS AND USAGE

AMMONUL is a nitrogen binding agent indicated as adjunctive therapy for the treatment of acute hyperammonemia and associated encephalopathy in patients with deficiencies in enzymes of the urea cycle. (1)

2 DOSAGE AND ADMINISTRATION

- AMMONUL must be diluted with sterile 10% Dextrose Injection (D10W) before administration. Administration must be through a central venous catheter. Administration through a peripheral line may cause burns. (2)
- AMMONUL is administered intravenously as a loading dose infusion administered over 90 to 120 minutes, followed by an equivalent maintenance dose infusion administered over 24 hours. (2)

3 DOSAGE FORMS AND STRENGTHS

Injection: 10% per 10% sterile, concentrated, aqueous solution of sodium phenylacetate and sodium benzoate. (3)

4 CONTRAINDICATIONS

None (4)

5 WARNINGS AND PRECAUTIONS

- Management of Acute Hyperammonemia: Monitor plasma ammonia levels during treatment. Prolonged exposure to elevated plasma ammonia levels can rapidly result in injury to the brain or death. Prompt use of all therapies necessary to reduce plasma ammonia levels is essential. (5.1)
- Decreased Potassium Levels: Plasma potassium levels should be carefully monitored and appropriate treatment given when necessary. (5.2)
- Conditions Associated with Fluid Overload: AMMONUL contains 30.5 mg of sodium per mL of undiluted product. Caution should be used if AMMONUL is administered to patients with congestive heart failure, severe renal insufficiency, or with conditions in which there is sodium retention with edema. (5.3)
- Extravasation: Extravasation of AMMONUL into the perivenous tissues during high flow bolus infusion may lead to skin necrosis, especially in infants. The infusion site must be monitored closely for possible tissue infiltration during drug administration. (5.4)
- Neurotoxicity of Phenylacetate: Because of prolonged plasma levels achieved by phenylacetate in pharmacokinetic studies, repeat loading doses should not be administered. Additionally, neurotoxicity related to phenylacetate has been reported in cancer patients. Monitor patients for symptoms of acute neurotoxicity.(5.5)
- Hyperventilation and Metabolic Acidosis: AMMONUL may cause side effects typically associated with salicylate overdose, such as hyperventilation and metabolic acidosis. Monitor patient blood chemistry profiles and perform frequent blood pH and pCO2 measurements. (5.6)

6 ADVERSE REACTIONS

The most frequently reported adverse reactions (incidence ≥ 6%) are vomiting, hyperglycemia, hypokalemia, convulsions, and mental impairment. (6)

To report SUSPECTED ADVERSE REACTIONS, contact Ucyclyd Pharma, Inc. at 1-800-321-4576 or FDA at 1-800-FDA-1088 or www.fda.gov/medwatch.

7 DRUG INTERACTIONS

- Some antibiotics such as penicillin may affect the overall disposition of the infused drug. (7)
- Probenecid may affect renal excretion of phenylacetylglutamine and hippurate. (7)
- Valproic acid given to patients with urea cycle disorders may exacerbate their condition and antagonize the efficacy of AMMONUL through inhibition of the synthesis of N-acetylglutamate, a co-factor for carbamyl phosphate synthetase. (7)
- Use of corticosteroids may cause the breakdown of body protein and potentially increase plasma ammonia levels in patients with impaired ability to form urea (7)

FULL PRESCRIBING INFORMATION

1 INDICATIONS AND USAGE

AMMONUL is indicated as adjunctive therapy in pediatric and adult patients for the treatment of acute hyperammonemia and associated encephalopathy in patients with deficiencies in enzymes of the urea cycle. During acute hyperammonemic episodes, arginine supplementation, caloric supplementation, dietary protein restriction, hemodialysis, and other ammonia lowering therapies should be considered [ see Warnings and Precautions (5)].

2 DOSAGE AND ADMINISTRATION

2.1 Recommended Dose

AMMONUL must be diluted with sterile 10% Dextrose Injection (D10W) before administration. The dilution and dosage of AMMONUL are determined by weight for neonates, infants and young children, and by body surface area for larger patients, including older children, adolescents, and adults (Table 1).

Table 1 Dosage and Administration
Patient Population | Components of Infusion Solution AMMONUL must be diluted with sterile 10% Dextrose Injection at ≥ 25 mL/Kg before administration. |  | Dosage Provided
 | AMMONUL | Arginine HCl Injection, 10% | Sodium Phenylacetate | Sodium Benzoate | Arginine HCl
Patients 0 to 20 kg:
CPS and OTC Deficiency
Dose
Loading: over 90 to 120 minutes | 2.5 mL/kg | 2 mL/kg | 250 mg/kg | 250 mg/kg | 200 mg/kg
Maintenance: over 24 hours
ASS and ASL Deficiency
Dose
Loading: over 90 to 120 minutes | 2.5 mL/kg | 6 mL/kg | 250 mg/kg | 250 mg/kg | 600 mg/kg
Maintenance: over 24 hours
Patients > 20 kg:
CPS and OTC Deficiency
Dose
Loading: over 90 to 120 minutes | 55 mL/m^2 | 2 mL/kg | 5.5 g/m^2 | 5.5 g/m^2 | 200 mg/kg
Maintenance: over 24 hours
ASS and ASL Deficiency
Dose
Loading: over 90 to 120 minutes | 55 mL/m^2 | 6 mL/kg | 5.5 g/m^2 | 5.5 g/m^2 | 600 mg/kg
Maintenance: over 24 hours

2.2 Administration

AMMONUL is a concentrated solution and must be diluted before intravenous administration via a central venous catheter. Administration through a peripheral intravenous catheter may cause burns. AMMONUL may not be administered by any other route.

AMMONUL should be administered as a loading dose infusion over 90 to 120 minutes, followed by the same dose repeated as a maintenance infusion administered over 24 hours. Because of prolonged plasma levels achieved by phenylacetate in pharmacokinetic studies, repeat loading doses of AMMONUL should not be administered. Maintenance infusions may be continued until elevated plasma ammonia levels have been normalized or the patient can tolerate oral nutrition and medications. An antiemetic may be administered during AMMONUL infusion to aid control of infusion-associated nausea and vomiting. Administration of analogous oral drugs, such as sodium phenylbutyrate, should be terminated prior to AMMONUL infusion.

AMMONUL infusion should be started as soon as the diagnosis of hyperammonemia is made. Treatment of hyperammonemia also requires caloric supplementation and restriction of dietary protein. Non-protein calories should be supplied principally as glucose (8–10 mg/kg/min) with an intravenous fat emulsion added. Attempts should be made to maintain a caloric intake of greater than 80 kcal/kg/day. During and after infusion of AMMONUL, ongoing monitoring of the following clinical laboratory values is crucial: plasma ammonia, glutamine, quantitative plasma amino acids, blood glucose, electrolytes, venous or arterial blood gases, AST and ALT. On-going monitoring of the following clinical responses is also crucial to assess patient response to treatment: neurological status, Glasgow Coma Scale, tachypnea, CT or MRI scan or fundoscopic evidence of cerebral edema, and/or of gray matter and white matter damage. Hemodialysis should be considered in patients with severe hyperammonemia or who are not responsive to AMMONUL administration [ see Warnings and Precautions (5.1)]. In the non-neonatal study patient population treated with AMMONUL, dialysis was required in 13% of hyperammonemic episodes. Standard hemodialysis was the most frequently used dialysis method. High levels of ammonia can be reduced quickly when AMMONUL is used with hemodialysis, as the ammonia-scavenging of AMMONUL suppresses the production of ammonia from catabolism of endogenous protein and hemodialysis eliminates the ammonia and ammonia conjugates.

AMMONUL solutions are physically and chemically stable for up to 24 hours at room temperature and room lighting conditions. No compatibility information is presently available for AMMONUL infusion solutions except for Arginine HCl Injection, 10%, which may be mixed in the same container as AMMONUL. Other infusion solutions and drug products should not be administered together with AMMONUL infusion solution. AMMONUL solutions may be prepared in glass and PVC containers.

Arginine Administration

Intravenous arginine is an essential component of therapy for patients with carbamyl phosphate synthetase (CPS), ornithine transcarbamylase (OTC), argininosuccinate synthetase (ASS), or argininosuccinate lyase (ASL) deficiency. Because hyperchloremic acidosis may develop after high-dose arginine hydrochloride administration, chloride and bicarbonate levels should be monitored and appropriate amounts of bicarbonate administered.

In hyperammonemic infants with suspected, but unconfirmed urea cycle disorders, intravenous arginine should be given (6 mL/kg of Arginine HCl Injection 10%, over 90 minutes followed by the same dose given as a maintenance infusion over 24 hours). If deficiencies of ASS or ASL are excluded as diagnostic possibilities, the intravenous dose of arginine HCl should be reduced to 2 mL/kg/day Arginine HCl Injection 10%.

Converting To Oral Treatment

Once elevated ammonia levels have been reduced to the normal range, oral therapy, such as sodium phenylbutyrate, dietary management and maintenance protein restrictions should be started or reinitiated.

3 DOSAGE FORMS AND STRENGTHS

AMMONUL (sodium phenylacetate and sodium benzoate) Injection 10% per 10% is a sterile, concentrated, aqueous solution of sodium phenylacetate and sodium benzoate.

4 CONTRAINDICATIONS

None.

5 WARNINGS AND PRECAUTIONS

5.1 Management of Acute Hyperammonemia

Any episode of acute symptomatic hyperammonemia should be treated as a life-threatening emergency. Uncontrolled hyperammonemia can rapidly result in brain damage or death, and prompt use of all therapies necessary, including hemodialysis, to reduce ammonia levels is essential.

Hyperammonemic coma (regardless of cause) in the newborn infant should be aggressively treated while the specific diagnosis is pursued. Hemodialysis should be promptly initiated in all newborn patients. A blood flow rate of 150 mL/min/m^2 should be targeted (ammonia clearance [mL/min] is similar to the blood flow rate [mL/min] through the dialyzer). Clearance of ammonia is approximately ten times greater by hemodialysis than by peritoneal dialysis or hemofiltration. Exchange transfusion is ineffective in the management of hyperammonemia. Hemodialysis may be repeated until the plasma ammonia level is stable at normal or near normal levels.

Hyperammonemia due to urea cycle disorders should be managed in coordination with medical personnel experienced in metabolic disorders. Ongoing monitoring of plasma ammonia levels, neurological status, laboratory tests, and clinical response in patients receiving AMMONUL is crucial to assess patient response to treatment.

5.2 Decreased Potassium Levels

Because urine potassium loss is enhanced by the excretion of the non-reabsorbable anions, phenylacetylglutamine and hippurate, plasma potassium levels should be carefully monitored and appropriate treatment given when necessary.

5.3 Conditions Associated with Fluid Overload

AMMONUL contains 30.5 mg of sodium per mL of undiluted product. Thus, AMMONUL should be used with great care, if at all, in patients with congestive heart failure or severe renal insufficiency, and in clinical states in which there is sodium retention with edema. Discontinue administration of AMMONUL, evaluate the patient, and institute appropriate therapeutic countermeasures if an adverse event occurs.

5.4 Extravasation

Administration must be through a central line. Administration through a peripheral line may cause burns. Bolus infusion flow rates are relatively high, especially for infants [ see Dosage and Administration (2)]. Extravasation of AMMONUL into the perivenous tissues may lead to skin necrosis. If extravasation is suspected, discontinue the infusion and resume at a different infusion site, if necessary. The infusion site must be monitored closely for possible infiltration during drug administration. Do not administer undiluted product.

5.5 Neurotoxicity of Phenylacetate

Because of prolonged plasma levels achieved by phenylacetate in pharmacokinetic studies, repeat loading doses of AMMONUL should not be administered. Additionally, neurotoxicity was reported in cancer patients receiving intravenous phenylacetate, 250–300 mg/kg/day for 14 days, repeated at 4-week intervals. Manifestations were predominantly somnolence, fatigue, and lightheadedness, with less frequent headaches, dysgeusia, hypoacusis, disorientation, impaired memory, and exacerbation of a pre-existing neuropathy. The acute onset of symptoms upon initiation of treatment and reversibility of symptoms when the phenylacetate was discontinued suggest a drug effect. [See Animal Toxicology and/or Pharmacology (13.2)]

5.6 Hyperventilation and Metabolic Acidosis

Due to structural similarities between phenylacetate and benzoate to salicylate, AMMONUL may cause side effects typically associated with salicylate overdose, such as hyperventilation and metabolic acidosis. Monitoring of blood chemistry profiles, blood pH and pCO2 should be performed.

6 ADVERSE REACTIONS

6.1 Clinical Trials Experience

Because clinical trials are conducted under widely varying conditions, adverse reaction rates observed in the clinical trials of a drug cannot be directly compared to rates in the clinical trials of another drug and may not reflect the rates observed in clinical practice.

The safety data were obtained from 316 patients who received AMMONUL as emergency (rescue) or prospective treatment for hyperammonemia as part of an uncontrolled, open-label study. The study population included patients between the ages of 0 to 53 years with a mean (SD) of 6.2 (8.54) years; 51% were male and 49% were female who had the following diagnoses: OTC (46%), ASS (22%), CPS (12%), ASL (2%), ARG (< 1%), THN (< 1%), and other (18%).

Table 2. Adverse Reactions Occurring in ≥ 3% of Patients Treated with AMMONUL
 | Patients N=316
Number of patients with any adverse event | 163 (52%)
Blood and lymphatic system disorders | 35 (11%)
Anemia | 12 (4%)
Disseminated intravascular coagulation | 11 (3%)
Cardiac disorders | 28 (9%)
Gastrointestinal disorders | 42 (13%)
Diarrhea | 10 (3%)
Nausea | 9 (3%)
Vomiting | 29 (9%)
General disorders and administration-site conditions | 45 (14%)
Injection-site reaction | 11 (3%)
Pyrexia | 17 (5%)
Infections | 39 (12%)
Urinary tract infection | 9 (3%)
Injury, poisoning and procedural complications | 12 (4%)
Investigations | 32 (10%)
Metabolism and nutrition disorders | 67 (21%)
Acidosis | 8 (3%)
Hyperammonemia | 17 (5%)
Hyperglycemia | 22 (7%)
Hypocalcemia | 8 (3%)
Hypokalemia | 23 (7%)
Metabolic acidosis | 13 (4%)
Nervous system disorders | 71 (22%)
Brain edema | 17 (5%)
Coma | 10 (3%)
Convulsions | 19 (6%)
Mental impairment | 18 (6%)
Psychiatric disorders | 16 (5%)
Agitation | 8 (3%)
Renal and urinary disorders | 14 (4%)
Respiratory, thoracic and mediastinal disorders | 47 (15%)
Respiratory distress | 9 (3%)
Skin and subcutaneous tissue disorders | 19 (6%)
Vascular disorders | 19 (6%)
Hypotension | 14 (4%)

Adverse reactions were reported with similar frequency in patients with OTC, ASS, CPS, and diagnoses categorized as "other." Nervous system disorders were more frequent in patients with OTC and CPS, compared with patients with ASS and patients with "other" diagnoses. Convulsions and mental impairment were reported in patients with OTC and CPS. These observations are consistent with literature reports that patients with enzyme deficiencies occurring earlier in the urea cycle (i.e., OTC and CPS) tend to be more severely affected.

Adverse reactions profiles differed by age group. Patients ≤ 30 days of age had more blood and lymphatic system disorders and vascular disorders (specifically hypotension), while patients > 30 days of age had more gastrointestinal disorders (specifically nausea, vomiting and diarrhea).

Less common adverse reactions (< 3% of patients) that are characterized as severe are listed below by body system.

BLOOD AND LYMPHATIC SYSTEM DISORDERS: coagulopathy, pancytopenia, thrombocytopenia

CARDIAC DISORDERS: atrial rupture, bradycardia, cardiac or cardiopulmonary arrest/failure, cardiogenic shock, cardiomyopathy, pericardial effusion

EYE DISORDERS: blindness

GASTROINTESTINAL DISORDERS: abdominal distension, gastrointestinal hemorrhage

GENERAL DISORDERS AND ADMINISTRATION-SITE CONDITIONS: asthenia, brain death, chest pain, multiorgan failure, edema

HEPATOBILIARY DISORDERS: cholestasis, hepatic artery stenosis, hepatic failure/hepatotoxicity, jaundice

INFECTIONS AND INFESTATIONS: sepsis/septic shock

INJURY, POISONING AND PROCEDURAL COMPLICATIONS: brain herniation, subdural hematoma, overdose

INVESTIGATIONS: blood carbon dioxide changes, blood glucose changes, blood pH increased, cardiac output decreased, pCO2 changes, respiratory rate increased

METABOLISM AND NUTRITION DISORDERS: alkalosis, dehydration, fluid overload/retention, hypoglycemia, hyperkalemia, hypernatremia, alkalosis, tetany

NEOPLASMS BENIGN, MALIGNANT AND UNSPECIFIED: hemangioma acquired

NERVOUS SYSTEM DISORDERS: areflexia, ataxia, brain infarction, brain hemorrhage, cerebral atrophy, clonus, depressed level of consciousness, encephalopathy, nerve paralysis, intracranial pressure increased, subdural hematoma, tremor

PSYCHIATRIC DISORDERS: acute psychosis, aggression, confusional state, hallucinations

RENAL AND URINARY DISORDERS: anuria, renal failure, urinary retention

RESPIRATORY, THORACIC AND MEDIASTINAL DISORDERS: acute respiratory distress syndrome, dyspnea, hypercapnia, hyperventilation, Kussmaul respiration, pneumonia aspiration, pneumothorax, pulmonary hemorrhage, pulmonary edema, respiratory acidosis or alkalosis, respiratory arrest/failure

SKIN AND SUBCUTANEOUS TISSUE DISORDERS: alopecia, blister, pruritis generalized, rash, urticaria

VASCULAR DISORDERS: flushing, hemorrhage, hypertension, phlebothrombosis/thrombosis

7 DRUG INTERACTIONS

Formal drug interaction studies have not been performed with AMMONUL.

Some antibiotics such as penicillin may compete with phenylacetylglutamine and hippurate for active secretion by renal tubules, which may affect the overall disposition of the infused drug.

Probenecid is known to inhibit the renal transport of many organic compounds, including aminohippuric acid, and may affect renal excretion of phenylacetylglutamine and hippurate.

There have been reports that valproic acid can induce hyperammonemia through inhibition of the synthesis of N-acetylglutamate, a co-factor for carbamyl phosphate synthetase. Therefore, administration of valproic acid to patients with urea cycle disorders may exacerbate their condition and antagonize the efficacy of AMMONUL.

Use of corticosteroids may cause a protein catabolic state and, thereby, potentially increase plasma ammonia levels in patients with impaired ability to form urea.

8 USE IN SPECIFIC POPULATIONS

8.1 Pregnancy

TERATOGENIC EFFECTS

Pregnancy Category C. Animal reproduction studies have not been conducted with AMMONUL. It is not known whether AMMONUL can cause fetal harm when administered to a pregnant woman or can affect reproduction capacity. Thus, AMMONUL should be given to a pregnant woman only if clearly needed.

8.3 Nursing Mothers

It is not known whether sodium phenylacetate, sodium benzoate, or their conjugation products are excreted in human milk. Because many drugs are excreted in human milk, caution should be exercised when AMMONUL is administered to a nursing woman.

8.4 Pediatric Use

AMMONUL has been used as a treatment for acute hyperammonemia in pediatric patients including patients in the early neonatal period [ see Dosage and Administration (2)].

8.5 Geriatric Use

Clinical studies of AMMONUL did not include any patients aged 65 and over to determine whether they respond differently from younger patients. Urea cycle disorders are presently diseases of the pediatric and younger adult populations. No pharmacokinetic studies of AMMONUL have been performed in geriatric patients. In general, dose selection for an elderly patient should be cautious, usually starting at the low end of the dosing range, reflecting the greater frequency of decreased hepatic, renal, or cardiac function, and concomitant disease or other drug therapy in this patient population.

8.6 Gender

Pharmacokinetic parameters of AMMONUL were compared in healthy males and females. Bioavailability of both benzoate and phenylacetate was slightly higher in females than in males. However, conclusions cannot be drawn due to the limited number of subjects in this study.

8.7 Hepatic Insufficiency

Limited information is available on the metabolism and excretion of sodium phenylacetate and sodium benzoate in patients with impaired hepatic function. However, metabolic conjugation of sodium phenylacetate and sodium benzoate is known to take place in the liver and kidney. Therefore, caution should be used in administering AMMONUL to patients with hepatic insufficiency.

8.8 Renal Impairment

The drug metabolites of AMMONUL (phenylacetylglutamine and hippurate) and subsequently ammonia are primarily excreted by the kidney. Therefore, use caution and closely monitor patients with impaired renal function who receive AMMONUL.

10 OVERDOSAGE

Overdosage has been reported during AMMONUL treatment in urea cycle-deficient patients. All patients in the uncontrolled open-label study were to be treated with the same dose of AMMONUL. However, some patients received more than the dose level specified in the protocol. In 16 of the 64 deaths, the patient received a known overdose of AMMONUL. Causes of death in these patients included cardiorespiratory failure/arrest (6 patients), hyperammonemia (3 patients), increased intracranial pressure (2 patients), pneumonitis with septic shock and coagulopathy (1 patient), error in dialysis procedure (1 patient), respiratory failure (1 patient), intractable hypotension and probable sepsis (1 patient), and unknown (1 patient). Additionally, other signs of intoxication may include obtundation (in the absence of hyperammonemia), hyperventilation, a severe compensated metabolic acidosis, perhaps with a respiratory component, large anion gap, hypernatremia and hyperosmolarity, progressive encephalopathy, cardiovascular collapse, and death.

In case of overdose of AMMONUL, discontinue the drug and institute appropriate emergency medical monitoring and procedures. In severe cases, the latter may include hemodialysis (procedure of choice) or peritoneal dialysis (when hemodialysis is unavailable).

11 DESCRIPTION

AMMONUL (sodium phenylacetate and sodium benzoate) Injection 10% per 10% (a nitrogen binding agent), is a sterile, concentrated, aqueous solution of sodium phenylacetate and sodium benzoate. The pH of the solution is between 6 and 8. Sodium phenylacetate is a crystalline, white to off-white powder with a strong, offensive odor. It is soluble in water. Sodium benzoate is a white and odorless, crystalline powder that is readily soluble in water.

Figure 1

Sodium phenylacetate has a molecular weight of 158.13 and the molecular formula C8H7NaO2. Sodium benzoate has a molecular weight of 144.11 and the molecular formula C7H5NaO2.

Each mL of AMMONUL contains 100 mg of sodium phenylacetate and 100 mg of sodium benzoate, and Water for Injection. Sodium hydroxide and/or hydrochloric acid may have been used for pH adjustment.

AMMONUL injection is a sterile, concentrated solution intended for intravenous administration via a central line only after dilution [ see Dosage and Administration (2)].

12 CLINICAL PHARMACOLOGY

12.1 Mechanism of Action

Urea cycle disorders can result from decreased activity of any of the following enzymes: N-acetylglutamate synthetase (NAGS), carbamyl phosphate synthetase (CPS), argininosuccinate synthetase (ASS), ornithine transcarbamylase (OTC), argininosuccinate lyase (ASL), or arginase (ARG).

Sodium phenylacetate and sodium benzoate are metabolically active compounds that can serve as alternatives to urea for the excretion of waste nitrogen. Figure 2 is a schematic illustrating how the components of AMMONUL, phenylacetate and benzoate, provide an alternative pathway for nitrogen disposal in patients without a fully functioning urea cycle. Phenylacetate conjugates with glutamine in the liver and kidneys to form phenylacetylglutamine, via acetylation. Phenylacetylglutamine is excreted by the kidneys via glomerular filtration and tubular secretion. The nitrogen content of phenylacetylglutamine per mole is identical to that of urea (both contain two moles of nitrogen). Two moles of nitrogen are removed per mole of phenylacetate when it is conjugated with glutamine. Similarly, preceded by acylation, benzoate conjugates with glycine to form hippuric acid, which is rapidly excreted by the kidneys by glomerular filtration and tubular secretion. One mole of hippuric acid contains one mole of waste nitrogen. Thus, one mole of nitrogen is removed per mole of benzoate when it is conjugated with glycine

Figure 2

CPS = carbamyl phosphate synthetase;
OTC = ornithine transcarbamylase;
ASS = argininosuccinate synthetase;
ASL = argininosuccinate lyase;
ARG = arginase;
NAGS = N-acetylglutamate synthetase

12.2 Pharmacodynamics

In patients with hyperammonemia due to deficiencies in enzymes of the urea cycle, AMMONUL has been shown to decrease elevated plasma ammonia levels. These effects are considered to be the result of reduction in nitrogen overload through glutamine and glycine scavenging by AMMONUL in combination with appropriate dietary and other supportive measures.

12.3 Pharmacokinetics

The pharmacokinetics of intravenously administered AMMONUL was characterized in healthy adult volunteers. Both benzoate and phenylacetate exhibited nonlinear kinetics. Following 90 minute intravenous infusion mean AUClast for benzoate was 20.3, 114.9, 564.6, 562.8, and 1599.1 mcg/mL following doses of 1, 2, 3.75, 4, and 5.5 g/m^2, respectively. The total clearance decreased from 5.19 to 3.62 L/h/m^2 at the 3.75 and 5.5 g/m^2 doses, respectively.

Similarly, phenylacetate exhibited nonlinear kinetics following the priming dose regimens. AUClast was 175.6, 713.8, 2040.6, 2181.6, and 3829.2 mcg∙h/mL following doses of 1, 2, 3.75, 4, and 5.5 g/m^2, respectively. The total clearance decreased from 1.82 to 0.89 mcg∙h/mL with increasing dose (3.75 and 4 g/m^2, respectively).

During the sequence of 90 minute priming infusion followed by a 24 hour maintenance infusion, phenylacetate was detected in the plasma at the end of infusion (Tmax of 2 hr at 3.75 g/m^2) whereas, benzoate concentrations declined rapidly (Tmax of 1.5 hr at 3.75 g/m^2) and were undetectable at 14 and 26 hours following the 3.75 and 4 g/m^2 dose, respectively.

A difference in the metabolic rates for phenylacetate and benzoate was noted. The formation of hippurate from benzoate occurred more rapidly than that of phenylacetylglutamine from phenylacetate, and the rate of elimination for hippurate appeared to be more rapid than that for phenylacetylglutamine.

Pharmacokinetic observations have also been reported from twelve episodes of hyperammonemic encephalopathy in seven children diagnosed (age 3 to 26 months) with urea cycle disorders who had been administered AMMONUL intravenously. These data showed peak plasma levels of phenylacetate and benzoate at approximately the same times as were observed in healthy adults. As in healthy adults, the plasma levels of phenylacetate were higher than benzoate and were present for a longer time.

The pharmacokinetics of intravenous phenylacetate have been reported following administration to adult patients with advanced solid tumors. The decline in serum phenylacetate concentrations following a loading infusion of 150 mg/kg was consistent with saturable enzyme kinetics. Ninety-nine percent of administered phenylacetate was excreted as phenylacetylglutamine [2,3].

13 NONCLINICAL TOXICOLOGY

13.1 Carcinogenesis, Mutagenesis, Impairment of Fertility

Long-term studies in animals have not been performed to evaluate the carcinogenic potential of AMMONUL. Studies to evaluate the possible impairment of fertility or mutagenic potential of AMMONUL have not been performed. Results indicate that sodium benzoate is not mutagenic or carcinogenic, and does not impair fertility.

13.2 Animal Toxicology and/or Pharmacology

In animal studies, subcutaneous administration to rat pups of 190–474 mg/kg of phenylacetate caused decreased proliferation and increased loss of neurons, and reduced central nervous system (CNS) myelin. Cerebral synapse maturation was retarded, and the number of functioning nerve terminals in the cerebrum was reduced, which resulted in impaired brain growth. Pregnant rats were given phenylacetate at 3.5 µmol/g/day subcutaneously from gestation day 7 through normal delivery. Prenatal exposure of rat pups to phenylacetate produced lesions in layer 5 cortical pyramidal cells; dendritic spines were longer and thinner than normal and reduced in number.

14 CLINICAL STUDIES

The efficacy of AMMONUL in improving patient survival of acute hyperammonemic episodes was demonstrated in an analysis of 316 patients (1045 episodes of hospitalization) treated between 1981 and 2003.

The demographic characteristics and diagnoses of the patient population are shown in Table 3.

Table 3 Baseline Characteristics and Diagnoses of Study Population
 |  | Patients [For the summary at the patient level, data obtained at first episode used.] N=316
Gender | Male | 158 (51%)
 | Female | 150 (49%)
Age (years) | N | 310
 | Mean (SD) | 6.2 (8.54)
 | Min–Max | 0.0–53.0
Age groups | 0–30 days | 104 (34%)
 | 31 days–2 years | 55 (18%)
 | > 2–12 years | 90 (29%)
 | > 12–16 years | 30 (10%)
 | > 16 years | 31 (10%)
Enzyme | OTC | 146 (46%)
deficiency | ASS | 71 (22%)
 | CPS | 38 (12%)
 | ASL | 7 (2%)
 | ARG | 2 (< 1%)
 | THN | 2 (< 1%)
 | Other [Diagnosis unknown or pending (33 episodes), acidemia (14 episodes), HHH syndrome (6 episodes), carnitine translocase deficiency (4 episodes), liver disease (3 episodes), HMG CoA lyase deficiency (1 episode), non-ketotic hyperglycinemia (1 episode), suspected fatty acid oxidation deficiency (1 episode), and valproic-acid-induced hyperammonemia (1 episode).] | 56 (18%)
OTC = ornithine transcarbamylase deficiency;
ASS = argininosuccinate synthetase deficiency;
CPS = carbamyl phosphate synthetase deficiency;
ASL = argininosuccinate lyase deficiency;
ARG = arginase deficiency;
THN = transient hyperammonemia of the newborn

On admission to the hospital, patients with hyperammonemia and a suspected or confirmed urea cycle disorder (UCD) diagnosis were treated with a bolus dose of 0.25 g/kg (or 5.5 g/m^2) sodium phenylacetate + 0.25 g/kg (or 5.5 g/m^2) sodium benzoate over a period of 90 minutes to 6 hours, depending on the specific UCD. Infusions also contained arginine; the dose of arginine depended on the specific UCD. After completion of the bolus dose, maintenance infusions of the same dose over 24 hours were continued until the patient was no longer hyperammonemic or oral therapy could be tolerated. The mean (SD) duration of treatment was 4.6 (6.45) days per episode, and ranged from 1 to 72 days.

Survival was substantially improved after AMMONUL treatment compared with historical values (estimated 14% 1-year survival rate with dietary therapy alone) and with dialysis (estimated 43% survival of acute hyperammonemia) .

Eighty percent of patients (252 of 316) survived their last episode. Of the 64 patients who died, 53 (83%) died during their first hyperammonemic episode. Of the 104 neonates (< 30d) treated with AMMONUL, 34 (33%) died during the first hyperammonemic episode.

Ammonia levels decreased from very high levels (> 4 times the upper limit of normal [ULN]) to lower levels in 91% of episodes after treatment. In patients responding to therapy, mean ammonia concentrations decreased from 200.9 umol/L at hour zero to 101.6 umol/L within four hours of initiation of AMMONUL therapy and were maintained. Hemodialysis is recommended for those patients who's plasma ammonia levels fail to fall below 150 umol/L or by more than 40% within 4 to 8 hours after receiving AMMONUL. A shift from high (≤ 4 times ULN) to very high (> 4 times ULN) levels was observed in only 4% of the episodes.

Overall, investigators rated neurological status as improved, much improved, or the same in 93% of episodes, and overall status in response to treatment as improved, much improved, or the same in 97% of episodes. Recovery from coma was observed in 97% of episodes where coma was present at admission (111 of 114 episodes).

16 HOW SUPPLIED/STORAGE AND HANDLING

AMMONUL (sodium phenylacetate and sodium benzoate) Injection 10% per 10% is supplied in a single use glass vial.

NDC 62592-720-50 single use vial containing 50 mL of sodium phenylacetate and sodium benzoate injection 10% per 10%.

STORAGE AND HANDLING

Storage: Store at 25°C (77°F), excursions permitted to 15° - 30°C (59°- 86°F).

17 PATIENT COUNSELING INFORMATION

Physicians should advise patients and caregivers about the following for safe use of AMMONUL:

- When plasma ammonia levels have normalized, dietary protein intake can usually be increased with the goal of unrestricted protein intake.
- Caution should be exercised when AMMONUL is administered to a nursing woman.
- The most common adverse reactions are vomiting, hyperglycemia, hypokalemia, convulsions, and mental impairment.
- Generally BUPHENYL is stopped during the time AMMONUL is used.

Manufactured by:

Cangene bioPharma, Inc.
Baltimore, MD 21230

Manufactured for:

Ucyclyd Pharma, Inc., a wholly-owned subsidiary of Medicis Pharmaceutical Corp., 7720 N. Dobson Road, Scottsdale, AZ 85256

Processed in the USA with Foreign Ingredients

04100281

PACKAGE LABEL

PRINCIPAL DISPLAY PANEL - 50 mL Vial Carton

Ucyclyd
Pharma®

NDC 62592-720-50
Rx Only

AMMONUL®
(sodium phenylacetate and
sodium benzoate) Injection

10% / 10%

50 mL
For IV use only

Warning: Administration must be through a central line.
Administration through a peripheral line may cause burns.

Must be diluted before IV administration

Sterile, non-pyrogenic, single use vial